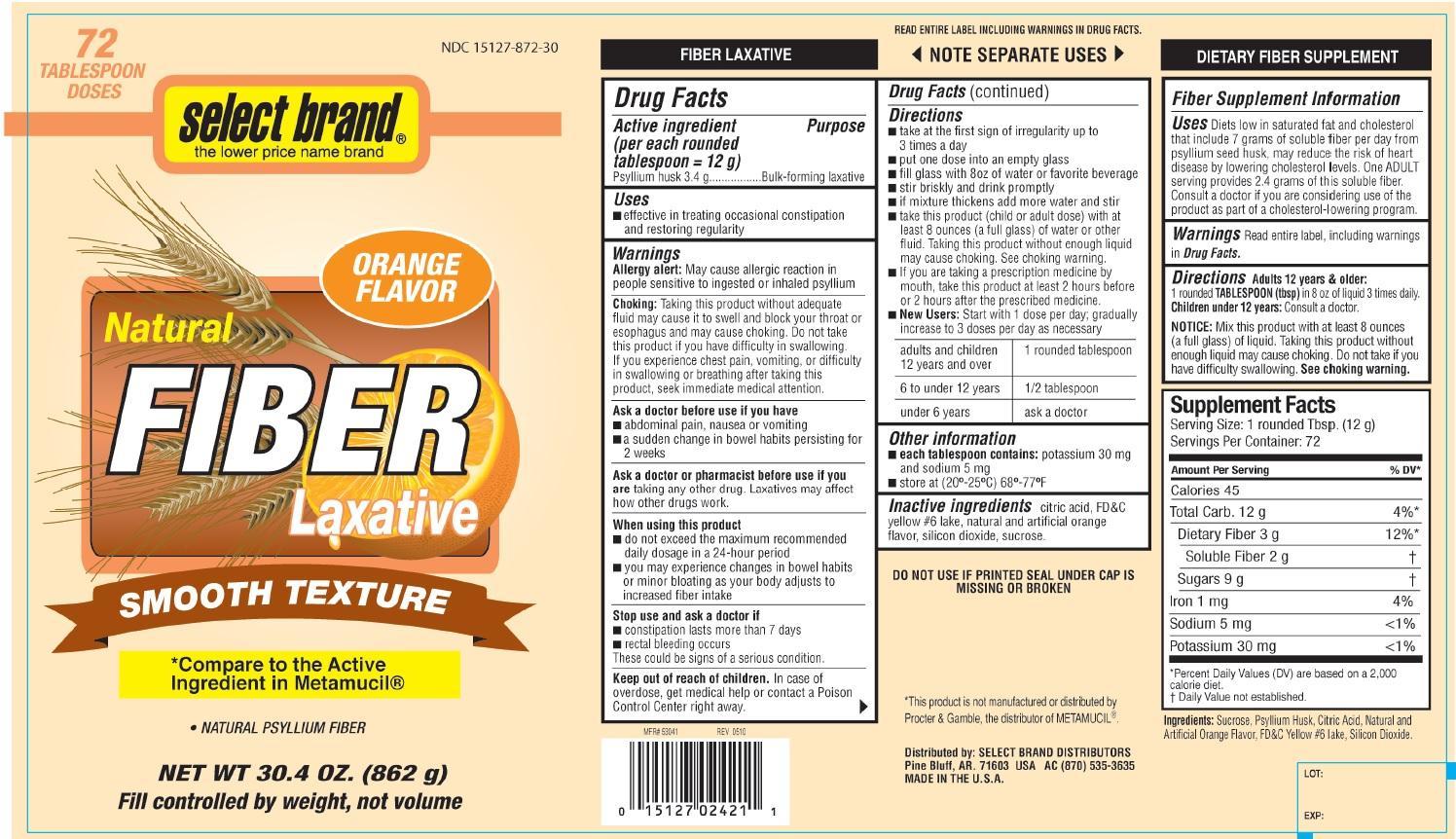 DRUG LABEL: Smooth texture Orange flavor
                
NDC: 15127-872 | Form: POWDER, FOR SUSPENSION
Manufacturer: Select Brand
Category: otc | Type: HUMAN OTC DRUG LABEL
Date: 20140903

ACTIVE INGREDIENTS: PSYLLIUM HUSK 3.4 g/12 g
INACTIVE INGREDIENTS: SUCROSE; ANHYDROUS CITRIC ACID; FD&C YELLOW NO. 6; SILICON DIOXIDE

Select Brand Smooth texture Orange Flavor Natural Fiber Laxative

Active ingredient (per each rounded tablespoon=12 g)

Psyllium husk 3.4 g

Purpose

Bulk-forming laxative

Uses

- effective in treating occasional constipation and restoring regularity

Warnings

Allergy alert: May cause allergic reaction in people sensitive to ingested or inhaled psyllium

Choking: Taking this product without adequate fluid may cause it to swell and block your throat or esophagus and may cause choking. Do not take this product if you have difficulty in swallowing. If you experience chest pain, vomiting, or difficulty in swallowing or breathing after taking this product, seek immediate medical attention.

Ask a doctor before use if you have

- abdominal pain, nausea or vomiting
- a sudden change in bowel habits persisting for 2 weeks

Ask a doctor or pharmacist before use if you are

taking any other drug. Laxatives may affect how other drugs work.

When using this product

- do not exceed the maximum recommended daily dosage in a 24-hour period
- you may experience changes in bowel habits or minor bloating as your body adjusts to increased fiber intake

Stop use and ask a doctor if

constipation lasts more than 7 days

rectal bleeding occurs

These could be signs of a serious condition.
Keep out of reach of children. In case of overdose, get medical help or contact a Poison Control Center right away.

Directions

- take at the first sign of irregularity up to 3 times a day
- put one dose into an empty glass
- fill glass with 8oz of water or favorite beverage
- stir briskly and drink promptly
- if mixture thickens add more water and stir
- take this product (child or adult dose) with at least 8 ounces (a full glass) of water or other fluid. Taking this product without enough liquid may cause choking. See choking warning.
- if you are taking a prescription medicine by mouth, take this product at least 2 hours before or 2 hours after the prescribed medicine.
- New Users: Start with 1 dose per day; gradually increase to 3 doses per day as necessary

adults and children 12 years and over | 1 rounded tablespoon
6 to under 12 years | 1/2 tablespoon
under 6 years | ask a doctor

Other information

- each tablespoon contains: potassium 30 mg and sodium 5 mg
- store at (20o-25oC) 68o-77oF

Inactive ingredients

citric acid, FD&C yellow 6, natural and artificial flavor, sucrose, silicon dioxide

DO NOT USE IF PRINTED SEAL UNDER CAP IS MISSING OR BROKEN

Fiber Supplement information

Uses Diets low in saturated fat and cholesterol that include 7 grams of soluble fiber per day from psyllium seed husk, may reduce the risk of heart disease by lowering cholesterol levels. One ADULT serving provides 2.4 grams of soluble fiber. Consult a doctor if you are considering use of the products as part of a cholesterol-lowering program.

Warnings Read entire label, including warnings in Drug Facts

Directions Adults 12 years and older: 1 rounded TABLESPOON (tbsp) in 8 oz of liquid 3 times daily.

Children under 12 years: Consult a doctor.

NOTICE: Mix this product with at least 8 ounces (a full glass) of liquid. Taking this product without enough liquid may cause choking. Do not take if you havbe difficulty swallowing. See choking warning.

PDP

Select Brand

Compare to the active ingredient in Metamucil®

Natural Fiber Laxative

Natural Psyllium Fiber

orange flavor smooth texture

net wt 30.4 OZ. (862 g) 72 tablespoon doses

Fill controlled by weight, not volume